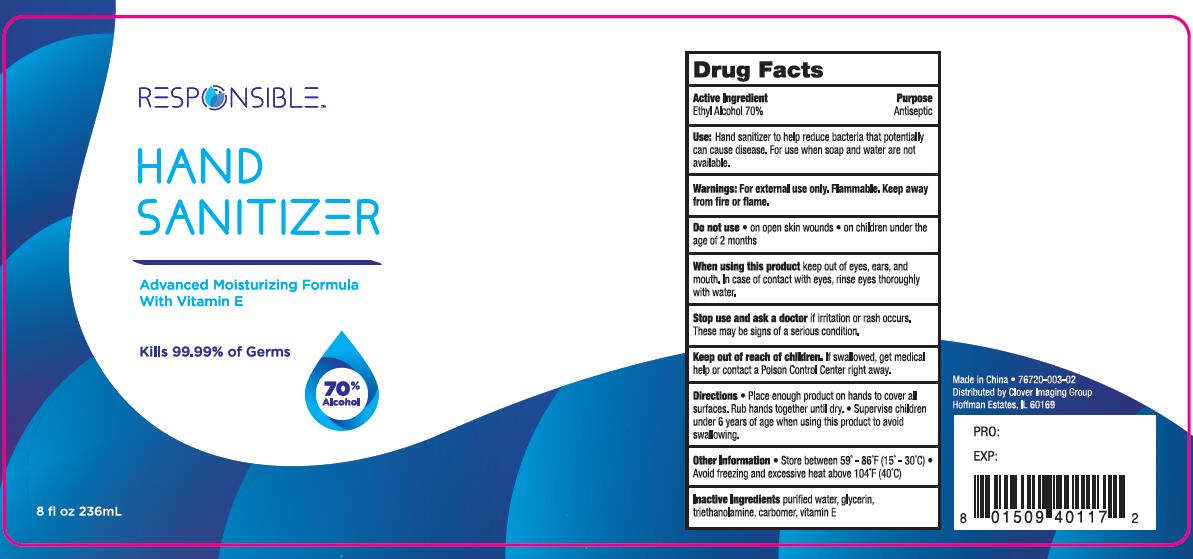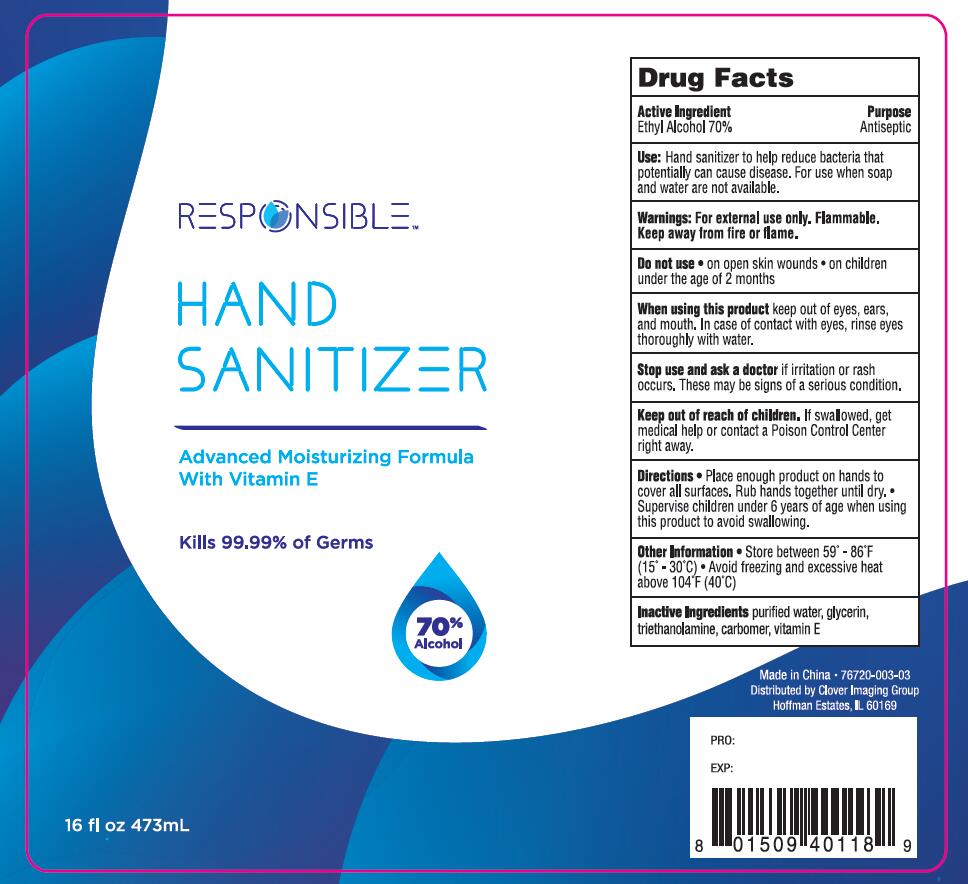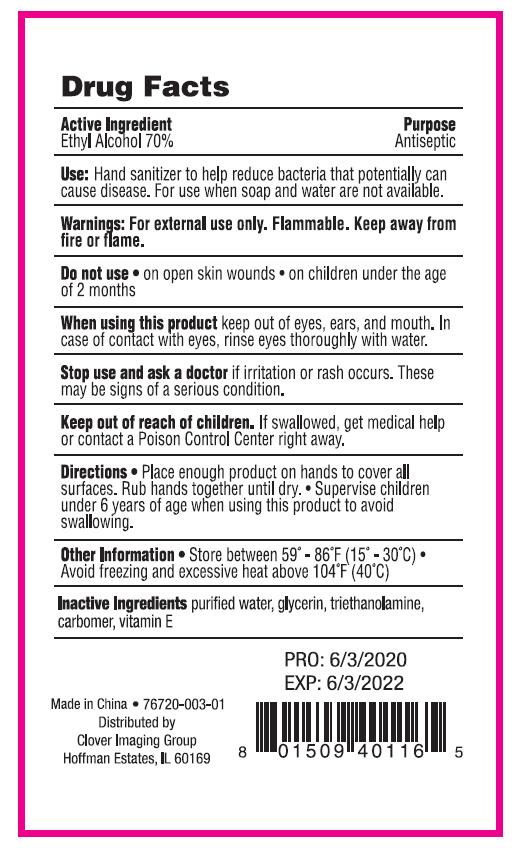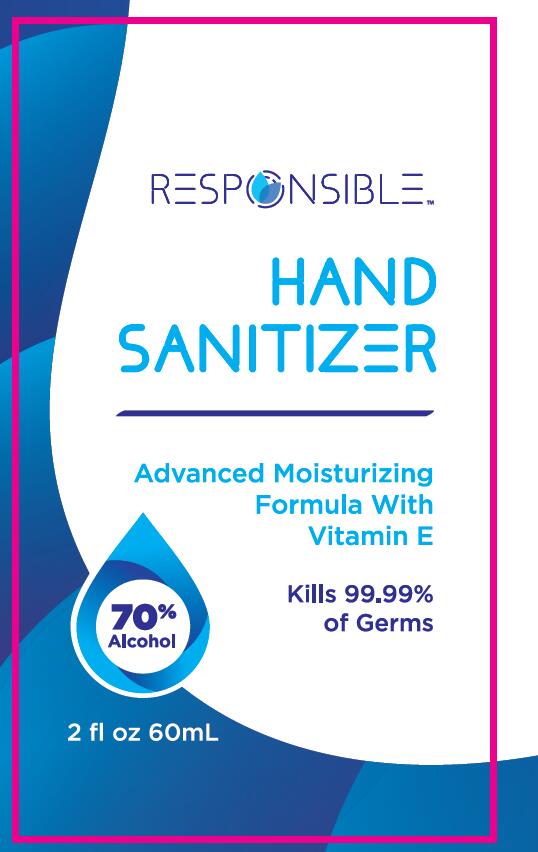 DRUG LABEL: HAND SANITIZER
NDC: 74763-003 | Form: GEL
Manufacturer: ZHEJIANG GAFLE AUTO CHEMICAL CO.,LTD
Category: otc | Type: HUMAN OTC DRUG LABEL
Date: 20220328

ACTIVE INGREDIENTS: ALCOHOL 70 mL/100 mL
INACTIVE INGREDIENTS: TROLAMINE; WATER; CARBOMER HOMOPOLYMER, UNSPECIFIED TYPE; GLYCERIN; .ALPHA.-TOCOPHEROL

HAND SANITIZER

ACTIVE INGERDIENT

Ethyl Alcohol 70%.

PURPOSE

Antiseptic

USES

Hand sanitizer to help reduce bacteria that potentially can cause disease. For use when soap and water are not available.

WARNINGS

For external use only.
Flammable. Keep away from heat or flame. Keep out of reach of children.
If swallowed, get medical help or contact
Poison Control Center right away.

DO NOT USE

on open skin wounds.
on children under the age of 2 months.

When using this product keep out of eyes, ears, and mouth. In case of contact with eyes, rinse eyes thoroughly with water.

Stop use and ask a doctor if irritation or rash occurs. These may be signs of a serious condition.

KEEP OUT OF REACH OF CHILDREN

If swallowed, get medical help or contact
Poison Control Center right away.

DIRECTIONS

Place enough product on hands to cover all surfaces.

Rub hands together until dry. Supervise children under 6 years of age when using this product to avoid swalloWing.

OTHER INFORMATION

store between 59°-86°F(15°-30°C)
Avoid treezing and excessive heat above 104°F(40 °C)

INACTIVE INGERDIENTS

Purified Water,Glycerin,Triethanolamine,Carbomer,Vitamin E.